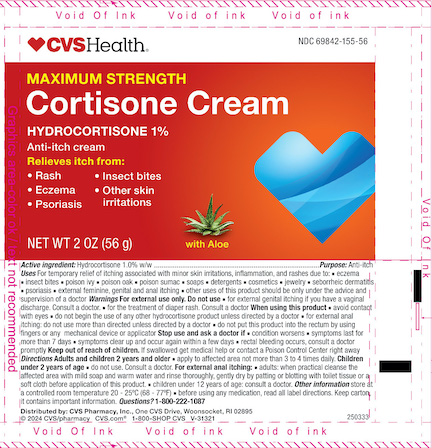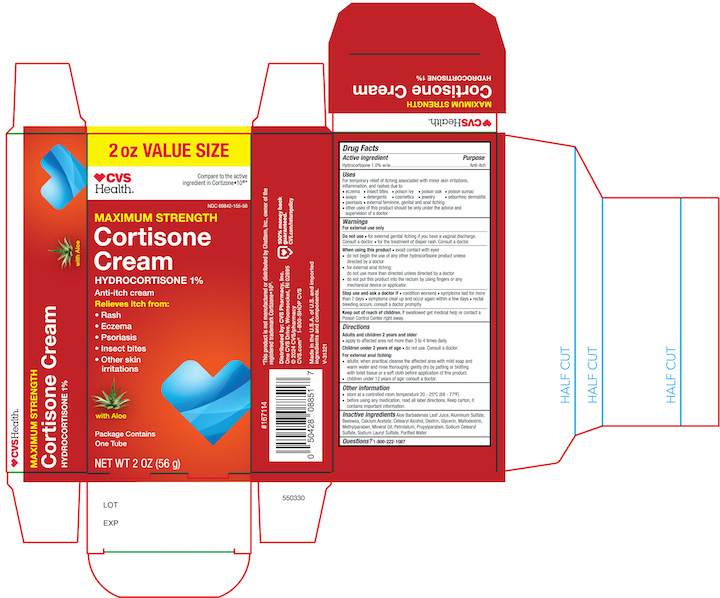 DRUG LABEL: CVS Health  Hydrocortisone Anti Itch
NDC: 69842-155 | Form: CREAM
Manufacturer: CVS Health
Category: otc | Type: HUMAN OTC DRUG LABEL
Date: 20240807

ACTIVE INGREDIENTS: Hydrocortisone 10 mg/1 g
INACTIVE INGREDIENTS: ALOE VERA LEAF; ALUMINUM SULFATE; YELLOW WAX; CALCIUM ACETATE; CETOSTEARYL ALCOHOL; GLYCERIN; ICODEXTRIN; MALTODEXTRIN; METHYLPARABEN; MINERAL OIL; PETROLATUM; PROPYLPARABEN; SODIUM CETOSTEARYL SULFATE; SODIUM LAURYL SULFATE; WATER

CVS Maximum Strength Cortisone Cream

Drug Facts

Active ingredient

Hydrocortisone 1.0%

Purpose

Anti-itch

Uses

For temporary relief of itching associated with minor skin irritations, inflammation, and rashes due to:

- eczema
- insect bites
- poison ivy
- poison oak
- poison sumac
- soaps
- detergents
- cosmetics
- jewelry
- seborrheic dermatitis
- psoriasis
- external feminine, genital and anal itching.

Other uses of this product should be only under the advice and supervision of a doctor.

Warnings

For external use only

Do not use

- for the treatment of diaper rash, consult a doctor.
- for external genital itching if you have a vaginal discharge, consult a doctor.

When using this product

- avoid contact with eyes
- do not begin the use of any other hydrocortisone product unless you have consulted a doctor.
- for external genital, feminine and anal itching do not exceed the recommended daily dosage unless directed by a doctor. In case of bleeding, stop use, consult a doctor.
- do not put this product into the rectum by using fingers or any mechanical device or applicator.

Stop use and ask a doctor if

- If condition worsens
- symptoms persist for more than 7 days or clear up and occur again within a few days, discontinue use of this product and do not begin use of any other hydrocortisone product unless directed by a doctor.

Keep out of reach of children. If swallowed get medical help or contact a Poison Control Center right away.

Directions

Adults and children 2 years and older

- apply to affected area not more than 3 to 4 times daily.

Children under 2 years of age

- do not use. Consult a doctor.

For external anal itching:

- adults: when practical cleanse the affected area with mild soap and warm water and rinse thoroughly or by patting or blotting with toilet tissue or a soft cloth before application of this product.
- children under 12 years of age with external anal itching: consult a doctor.

Other information

store at a controlled room temperature 20 - 25ºC (68 - 77ºF).

Inactive ingredients

Aloe barbadensis leaf extract, Aluminum Sulfate, Beeswax, Calcium acetate, Cetearly alcohol, Dextrin, Glycerin, Maltodextrin, Methylparaben, Mineral oil , Petrolatum, propylparaben, Sodium cetearyl sulfate, Sodium lauryl sulfate, Water (purified)

Principal display panel Tube and Carton Label

CVS Health

Maxmium Strength

Cortisone Cream 1%

Anti Itch

NET WT 2 OZ (56g)